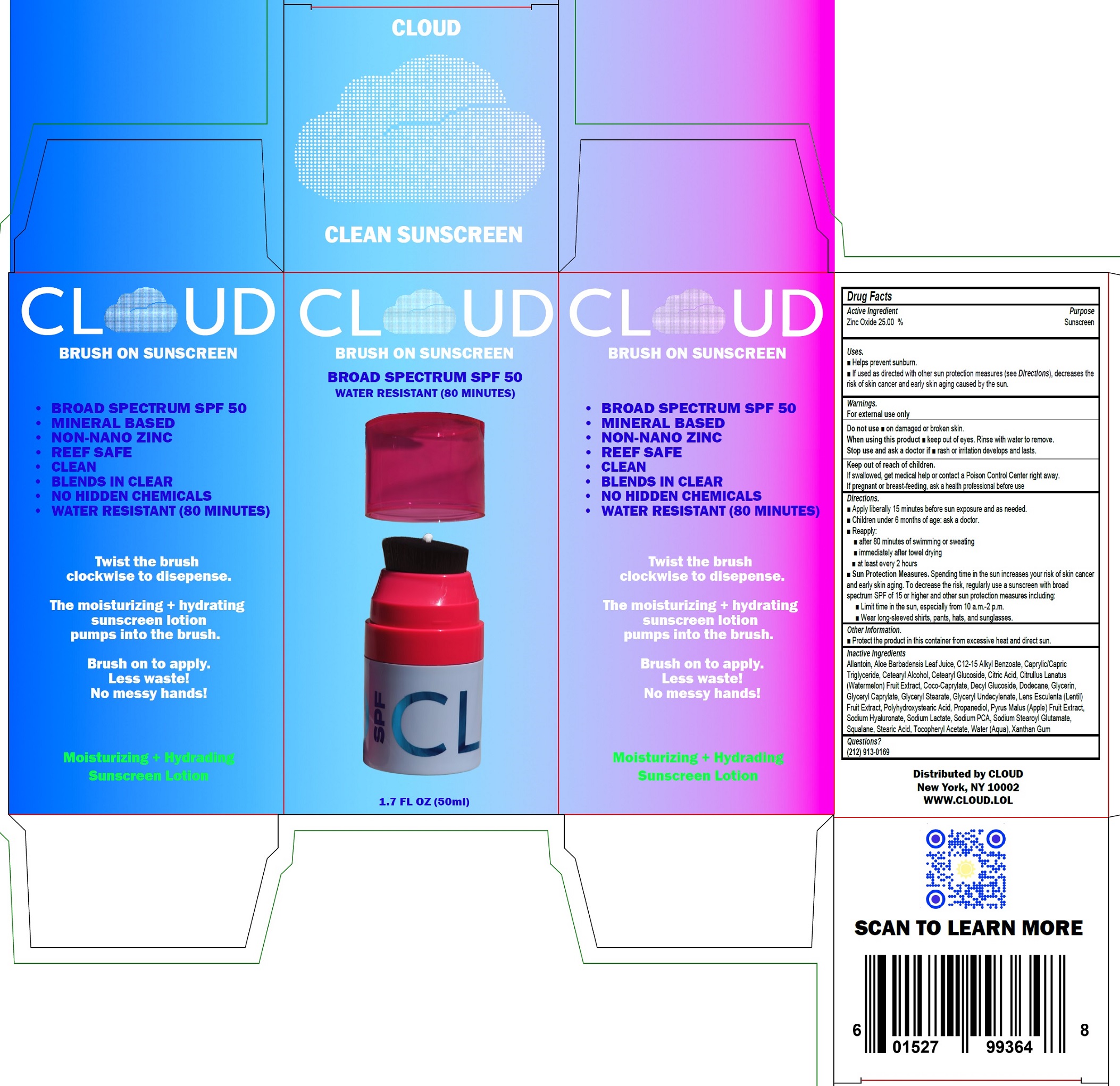 DRUG LABEL: Cloud Brush On Sunscreen SPF 50
NDC: 85678-897 | Form: CREAM
Manufacturer: FUTURE 8 LLC
Category: otc | Type: HUMAN OTC DRUG LABEL
Date: 20251013

ACTIVE INGREDIENTS: ZINC OXIDE 250 mg/1 mL
INACTIVE INGREDIENTS: ALLANTOIN; ALOE VERA LEAF JUICE; ALKYL (C12-15) BENZOATE; MEDIUM-CHAIN TRIGLYCERIDES; CETOSTEARYL ALCOHOL; CETEARYL GLUCOSIDE; CITRIC ACID MONOHYDRATE; WATERMELON; COCO-CAPRYLATE; DECYL GLUCOSIDE; DODECANE; GLYCERIN; GLYCERYL CAPRYLATE; GLYCERYL STEARATE; LENTIL; PROPANEDIOL; APPLE; SODIUM HYALURONATE; SODIUM LACTATE; SODIUM PYRROLIDONE CARBOXYLATE; SODIUM STEAROYL GLUTAMATE; SQUALANE; STEARIC ACID; .ALPHA.-TOCOPHEROL ACETATE; WATER; XANTHAN GUM

Cloud Brush On Sunscreen SPF 50

Active Ingredient

Zinc Oxide 25.00%

Purpose

Sunscreen

Uses.

- Helps prevent sunburn.
- If used as directed with other sun protection measures (see Directions), decreases the risk of skin cancer and early skin aging caused by the sun.

Warnings.

For external use only

Do not use

- on damaged or broken skin.

When using this product

- keep out of eyes. Rinse with water to remove.

Stop use and ask a doctor if

- rash or irritation develops and lasts.

Keep out of reach of children.

If swallowed, get medical help or contact a Poison Control Center right away.

If pregnant or breast-feeding,

ask a health professional before use

Directions.

- Apply liberally 15 minutes before sun exposure and as needed.
- Children under 6 months of age: ask a doctor.
- Reapply:
- after 80 minutes of swimming or sweating
- immediately after towel drying
- at least every 2 hours
- Sun Protection Measures. Spending time in the sun increases your risk of skin cancer and early skin aging. To decrease the risk, regularly use a sunscreen with broad spectrum SPF of 15 or higher and other sun protection measures including:
- Limit time in the sun, especially from 10 a.m - 2 p.m.
- Wear long-sleeved shirts, pants, hats, and sunglasses.

Other Information

- Protect the product in this container from excessive heat and direct sun.

Inactive Ingredients

Allantoin, Aloe Barbadensis Leaf Juice, C12-15 Alkyl Benzoate, Caprylic/Capric Triglyceride, Cetearyl Alcohol, Cetearyl Glucoside, Citric Acid, Citrullus Lanatus (Watermelon) Fruit Extract, Coco-Caprylate, Decyl Glucoside, Dodecane, Glycerin, Glyceryl Caprylate, Glyceryl Stearate, Glyceryl Undecylenate, Lens Esculenta (Lentil) Fruit Extract, Polyhydroxystearic Acid, Propanediol, Pyrus Malus (Apple) Fruit Extract, Sodium Hyaluronate, Sodium Lactate, Sodium PCA, Sodium Stearoyl Glutamate, Squalane, Stearic Acid, Tocopheryl Acetate, Water (Aqua), Xanthan Gum

Questions?

(212) 913-0169